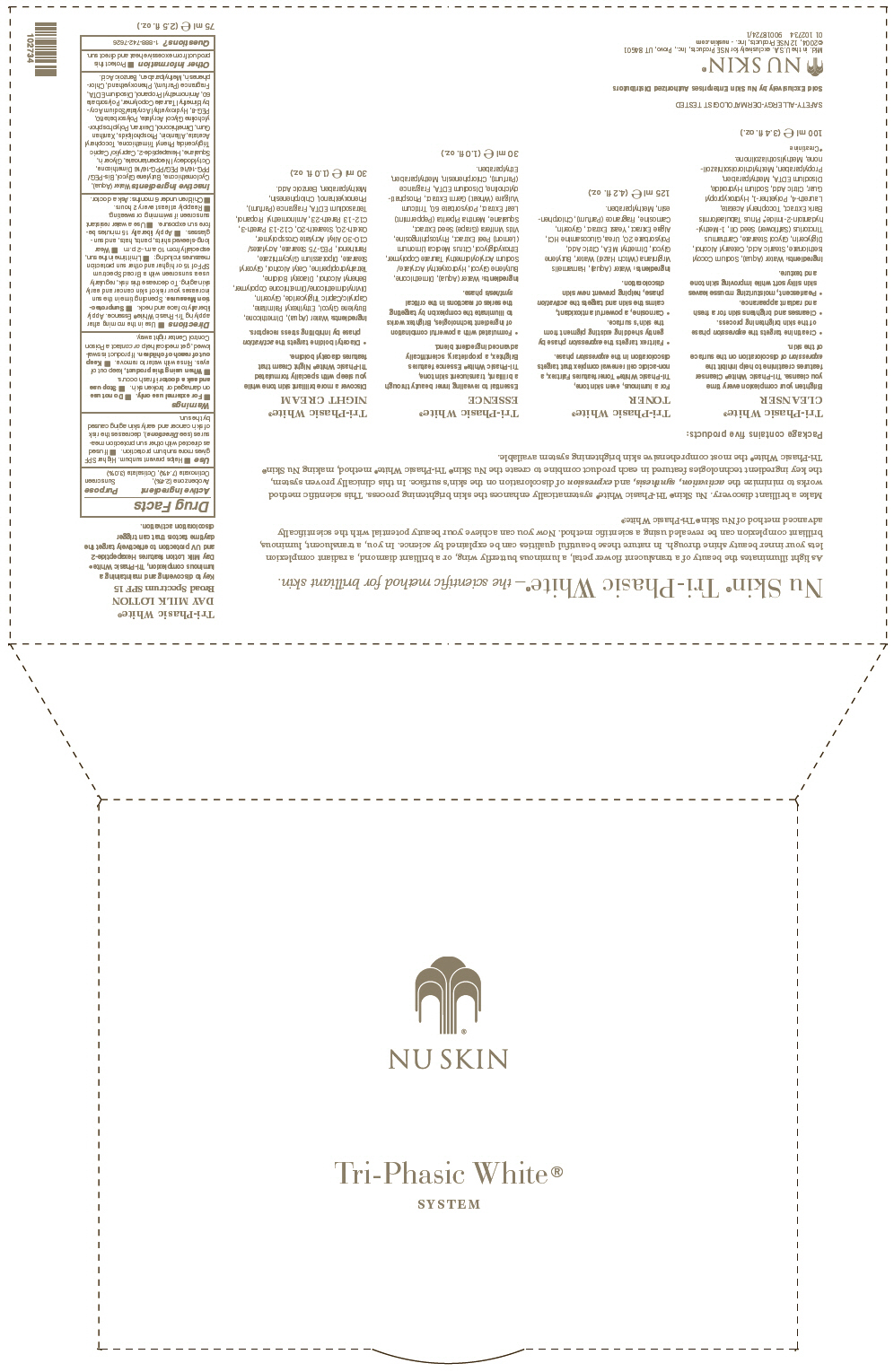 DRUG LABEL: Nu Skin Tri-Phasic White System
NDC: 62839-2734 | Form: KIT | Route: TOPICAL
Manufacturer: NSE Products, Inc.
Category: otc | Type: HUMAN OTC DRUG LABEL
Date: 20221219

ACTIVE INGREDIENTS: Avobenzone 24 mg/1 mL; Octinoxate 74 mg/1 mL; Octisalate 30 mg/1 mL
INACTIVE INGREDIENTS: Water; Cyclomethicone; Butylene Glycol; Octyldodecyl Neopentanoate; POLYETHYLENE GLYCOL 400; Phenyl Trimethicone; Phenoxyethanol; Medium-Chain Triglycerides; Polysorbate 80; Squalane; Xanthan Gum; Chlorphenesin; Glycerin; Allantoin; Edetate Disodium; Polysorbate 60; Methylparaben; Benzoic Acid; .Alpha.-Tocopherol Acetate; Aminomethylpropanol

Nu Skin Tri-Phasic White® System

Nu Skin® Tri-Phasic White® Day Milk Lotion Broad Spectrum SPF 15

Drug Facts

Active Ingredient

Avobenzone (2.4%), Octinoxate (7.4%), Octisalate (3.0%)

Purpose

Sunscreen

Use

- Helps prevent sunburn. Higher SPF gives more sunburn protection.
- If used as directed with other sun protection measures (see Directions), decreases the risk of skin cancer and early skin aging caused by the sun.

Warnings

- For external use only.

- Do not use on damaged or broken skin.

- Stop use and ask a doctor if rash occurs.

- When using this product, keep out of eyes. Rinse with water to remove.

- Keep out of reach of children. If product is swallowed, get medical help or contact a Poison Control Center right away.

Directions

- Use in the morning after applying Tri-Phasic White® Essence. Apply liberally to face and neck.
- Sunprotection Measures. Spending time in the sun increases your risk of skin cancer and early skin aging. To decrease this risk, regularly use a sunscreen with a Broad Spectrum SPF of 15 or higher and other sun protection measures including:
  - Limit time in the sun, especially from 10 a.m.–2 p.m.
  - Wear long-sleeved shirts, pants, hats, and sunglasses.
- Apply liberally 15 minutes before sun exposure.
- Use a water resistant sunscreen if swimming or sweating.
- Reapply at least every 2 hours.
- Children under 6 months: Ask a doctor.

Inactive Ingredients

Water (Aqua), Cyclomethicone, Butylene Glycol, Bis-PEG/PPG-16/16 PEG/PPG-16/16 Dimethicone, Octyldodecyl Neopentanoate, Glycerin, Squalane, Hexapeptide-2, Caprylic/ Capric Triglyceride, Phenyl Trimethicone, Tocopheryl Acetate, Allantoin, Phospholipids, Xanthan Gum, Dimethiconol, Dextran, Polyphosphorylcholine Glycol Acrylate, Polysorbate 80, PEG-8, Hydroxyethyl Acrylate/Sodium Acryloyldimethyl Taurate Copolymer, Polysorbate 60, Aminomethyl Propanol, Disodium EDTA, Fragrance (Parfum), Phenoxyethanol, Chlorphenesin, Methylparaben, Benzoic Acid.

Other Information

- Protect this product from excessive heat and direct sun.

Questions?

1-888-742-7626

PRINCIPAL DISPLAY PANEL - Kit Carton

NU SKIN

Tri-Phasic White®

SYSTEM